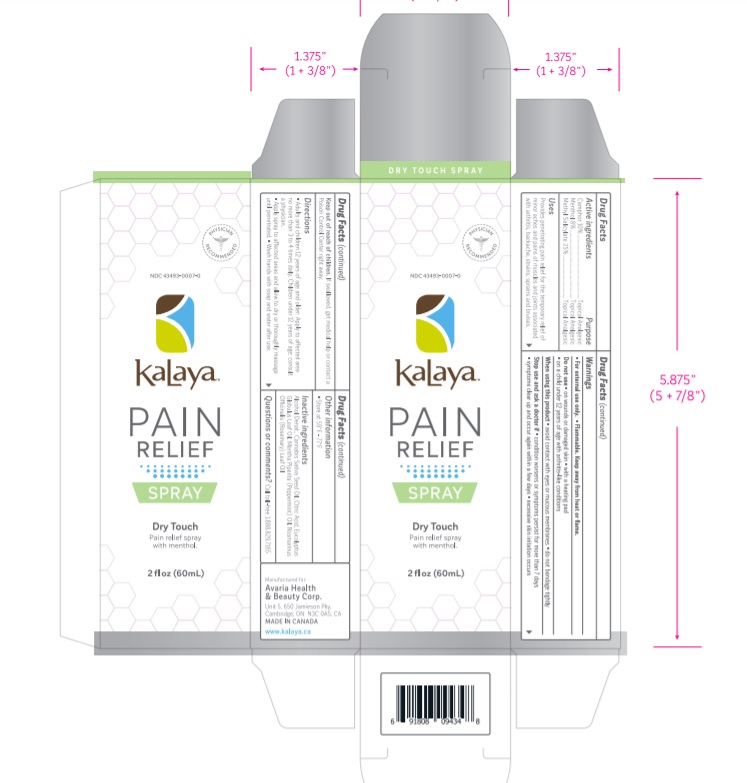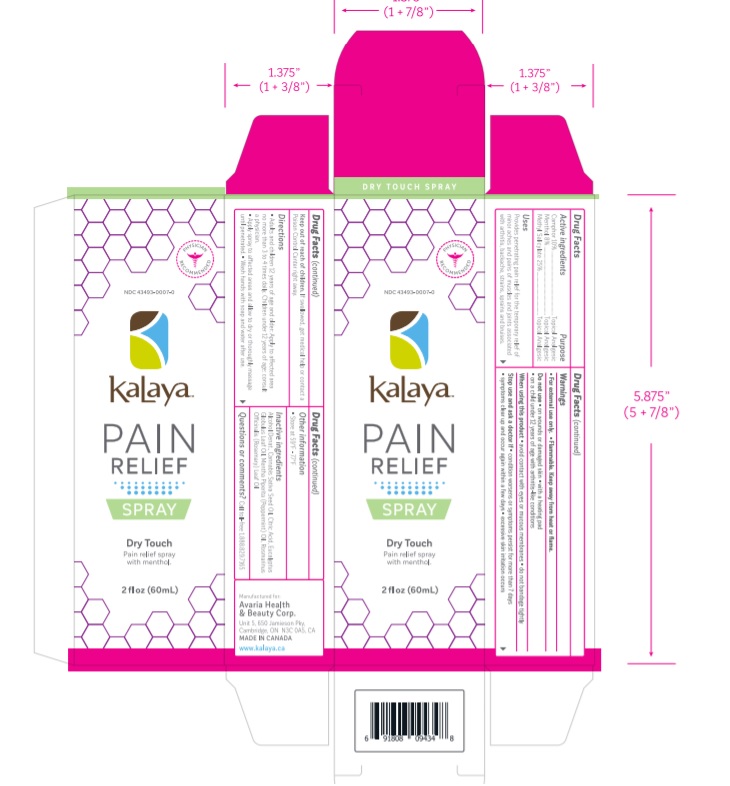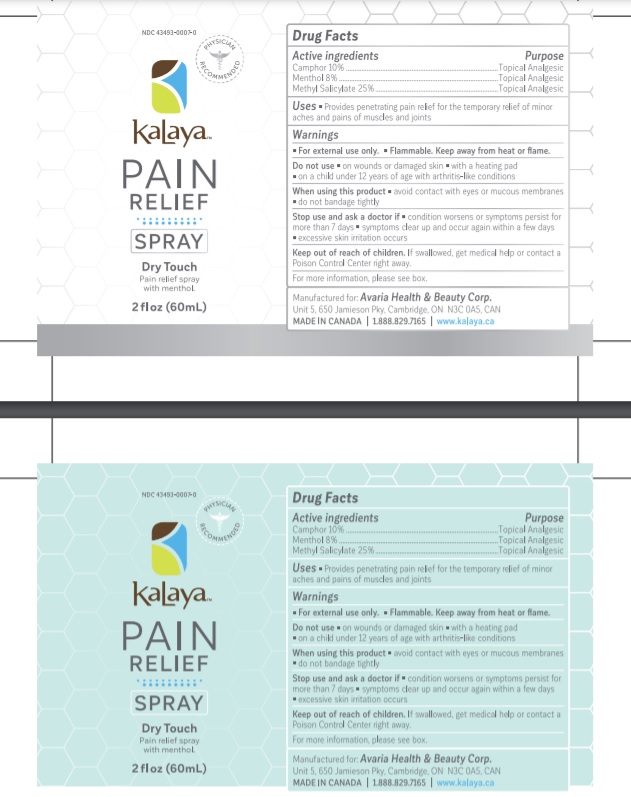 DRUG LABEL: Kalaya Pain Relief
NDC: 43493-0007 | Form: LIQUID
Manufacturer: Avaria Health & Beauty Corp
Category: otc | Type: HUMAN OTC DRUG LABEL
Date: 20251008

ACTIVE INGREDIENTS: MENTHOL 8 g/100 mL; CAMPHOR (SYNTHETIC) 10 g/100 mL; METHYL SALICYLATE 25 g/100 mL
INACTIVE INGREDIENTS: ALCOHOL; CANNABIS SATIVA SEED OIL; ANHYDROUS CITRIC ACID; EUCALYPTUS OIL; PEPPERMINT OIL; ROSEMARY OIL

Active ingredients

Camphor 10%,

Menthol 8%,

Methyl salicylate 25%

Purpose

Topical Analgesic

Uses

Provides penetrating pain relief for the temporary relief of minor aches and pains of muscles and joints

Warnings

For External Use Only. Flammable. Keep away from heat or flame.
Do not Use
• on wounds or damaged skin
• with a heating pad
• on a child under 12 years of age with arthritis-like conditions

When using this product avoid contact with eyes or mucous membranes, do not bandage tightly

Stop use and ask a doctor if condition worsen or symptoms persist more than 7 days, symptoms clear up and occur again within a few days

excessive skin irritation occurs.

Keep out of reach of children

If swallowed, get medical help or contact a Poison Control Center right away

Directions

Adults and children 12 years and over: Spray evenly onto affected areas no more than 3 to 4 times daily. Apply spray to affected areas and allowed to dry or thoroughly massage until penetrated. Wash hands with soap and water after use.

Other information

Store at 59°F - 77°F

Inactive ingredients

Alcohol Denat., Cannabis Sativa Seed Oil, Citric Acid, Eucalyptus Globulus Leaf Oil, Mentha Piperita (Peppermint) Oil, Rosmarinus Officinalis (Rosemary) Leaf Oil

Questions or comments?

Call toll-free 1.888.829.7165